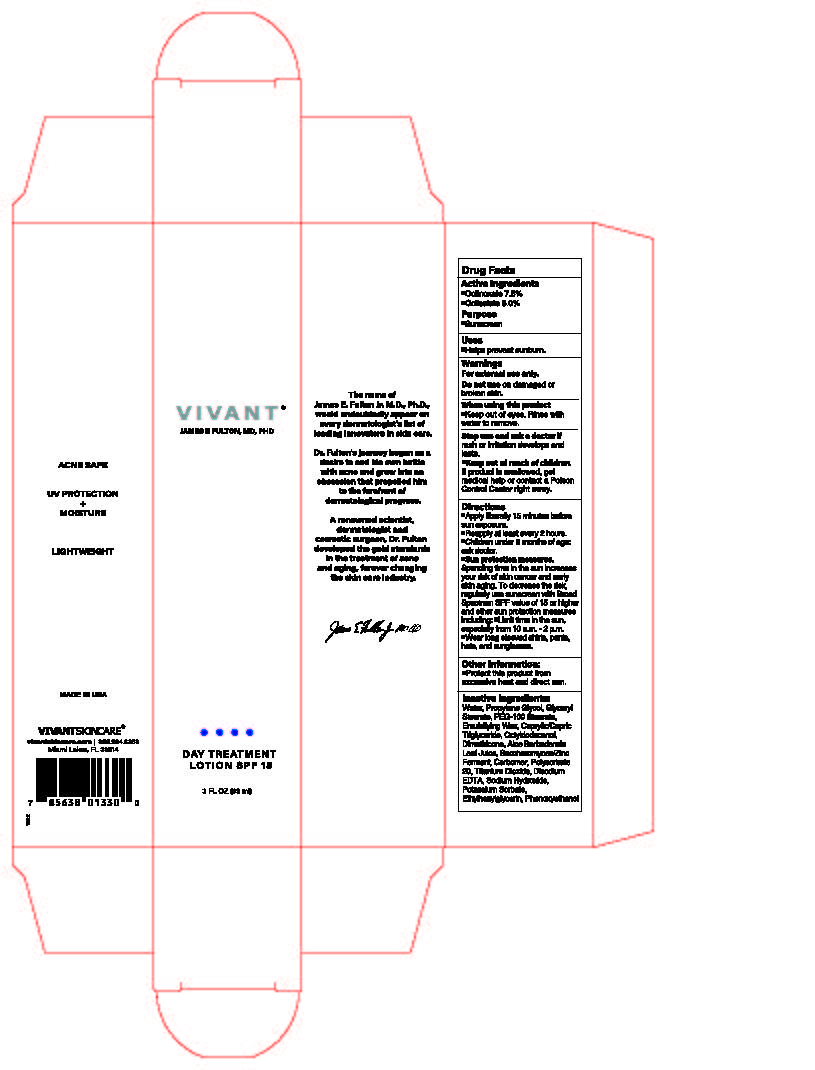 DRUG LABEL: Vivant Day Treatment SPF 15
NDC: 63750-015 | Form: LOTION
Manufacturer: Vivant Pharmaceuticals, LLC
Category: otc | Type: HUMAN OTC DRUG LABEL
Date: 20241105

ACTIVE INGREDIENTS: OCTINOXATE 7.5 g/100 mL; OCTISALATE 5 g/100 mL
INACTIVE INGREDIENTS: CETOSTEARYL ALCOHOL; PHENOXYETHANOL; SODIUM HYDROXIDE; POLYSORBATE 60; POLYSORBATE 20; ACRYLIC ACID; ETHYLHEXYLGLYCERIN; ALOE VERA LEAF; PEG-60 STEARATE; DIMETHICONE; MEDIUM-CHAIN TRIGLYCERIDES; GLYCERYL 1-STEARATE; TITANIUM DIOXIDE; POTASSIUM SORBATE; SACCHAROMYCES CEREVISIAE; EDETATE DISODIUM ANHYDROUS; WATER; OCTYLDODECANOL; PROPYLENE GLYCOL

Vivant Day Treatment SPF 15

Active ingredients Purpose
Octinoxate 7.5%.......................................................................Sunscreen
Octisalate 5.0%........................................................................Sunscreen

PURPOSE

Sunscreen

INDICATIONS AND USAGE

Uses• helps prevent sunburn

Warnings
For external use only
Do not useon damaged or broken skin

When using this product

Keep out of eyes. Rinse with water to remove.

Stop use and ask a doctor if rash or irritation develops and lasts.

Keep out of reach of children

If product is swallowed, get medical help or contact a Poison Control Center right away.

Directions

• apply liberally 15 minutes before sun exposure
• reapply at least every 2 hours

- Children under 6 months of age: ask a doctor.

• Sun Protection Measures. Spending time in the sun increases your
risk of skin cancer and early skin aging. To decrease this risk, regularly
use a sunscreen with a broad spectrum SPF of 15 or higher and other
sun protection measures including:
• limit time in the sun, especially from 10 a.m. – 2 p.m.
• wear long-sleeve shirts, pants, hats, and sunglasses

Other information

• protect this product from excessive heat and direct sun.

Inactive ingredients

Water, Propylene Glycol, Glyceryl Stearate, PEG-100 Stearate, Emulsifying Wax, Caprylic/Capric Triglyceride, Octyldodecanol, Dimethicone, Aloe Barbadensis Leaf Juice, Saccharomyces/Zinc Ferment, Carbomer, Polysorbate 20, Titanium Dioxide, Disodium EDTA, Sodium Hydroxide, Potassium Sorbate, Ethylhexylglycerin, Phenoxyethanol